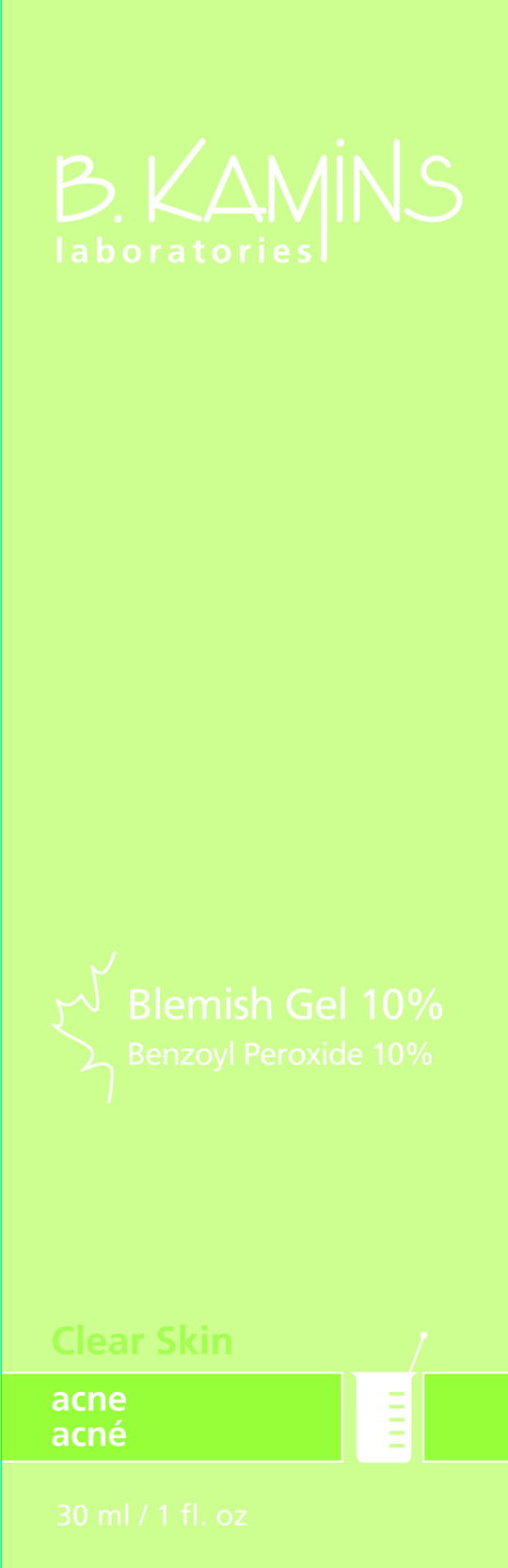 DRUG LABEL: BLEMISH
NDC: 63550-194 | Form: GEL
Manufacturer: Kamins Dermatologics Inc.
Category: otc | Type: HUMAN OTC DRUG LABEL
Date: 20101019

ACTIVE INGREDIENTS: BENZOYL PEROXIDE 100 mg/1 mL
INACTIVE INGREDIENTS: WATER; ACER SACCHARUM SAP; DIMETHICONE; SODIUM HYDROXIDE; PHENOXYETHANOL; CAPRYLYL GLYCOL; SORBIC ACID

BLEMISH GEL 10% CONSUMER LABELING

Active ingredients:
Benzoyl Peroxide: 10%

Purpose: Acne Treatment

Keep out of children’s reach.

INDICATIONS AND USAGE

A unique oil-free, color-free benzoyl peroxide gel that helps to gently clear blemishes, blackheads and spots. Also contains our moisturizing Bio-Maple compound, which helps prevent skin from becoming excessively dry.

Uses
■ Helps treat acne.

■ Dries up acne pimples.

■ Helps prevent new acne pimples.

Warnings
For external use only.

Do not use on

- broken skin.

- large areas of the body.

When using this product,

- Apply to affected areas only
- avoid unnecessary sun exposure and use a sunscreen
- avoid contact with eyes/eye area, lips, mouth and nostrils. If contact occurs, rinse thoroughly with water.
- This product may bleach hair or dyed fabrics.
- Using other topical acne drugs at the same time or right after use of this product may increase dryness or irritation of the skin. Only one drug should be used unless directed by a doctor.

Stop use and ask a doctor if too much skin irritation or sensitivity develops or increases.
If swallowed, seek medical assistance or contact a Poison Control Center immediately.

Directions

- Clean the skin thoroughly befor applying.
- Cover the entire affected area with a thin layer 1 to 3 times daily.
- because too much drying of the skin may occur, start with 1 application daily, then gradually increase to 2-3 times daily if needed or as directed by a doctor.
- If bothersome dryness or peeling occurs, reduce application to once a day or every other day.
- If going outside, use a sunscreen. Allow medicated acne gel to dry, then follow directions on the sunscreen labeling.

INACTIVE INGREDIENT

INACTIVE INGREDIENTS: water, alcohol denat., acer saccharum (maple isolate), disodium PEG-12 dimethicone sulfosuccinate, carbomer, sodium hydroxide, phenoxyethanol, caprylyl glycol, sorbic acid

PACKAGE LABEL

B. KAMINS

BLEMISH GEL 10%

30mL / 1.7 fl.oz